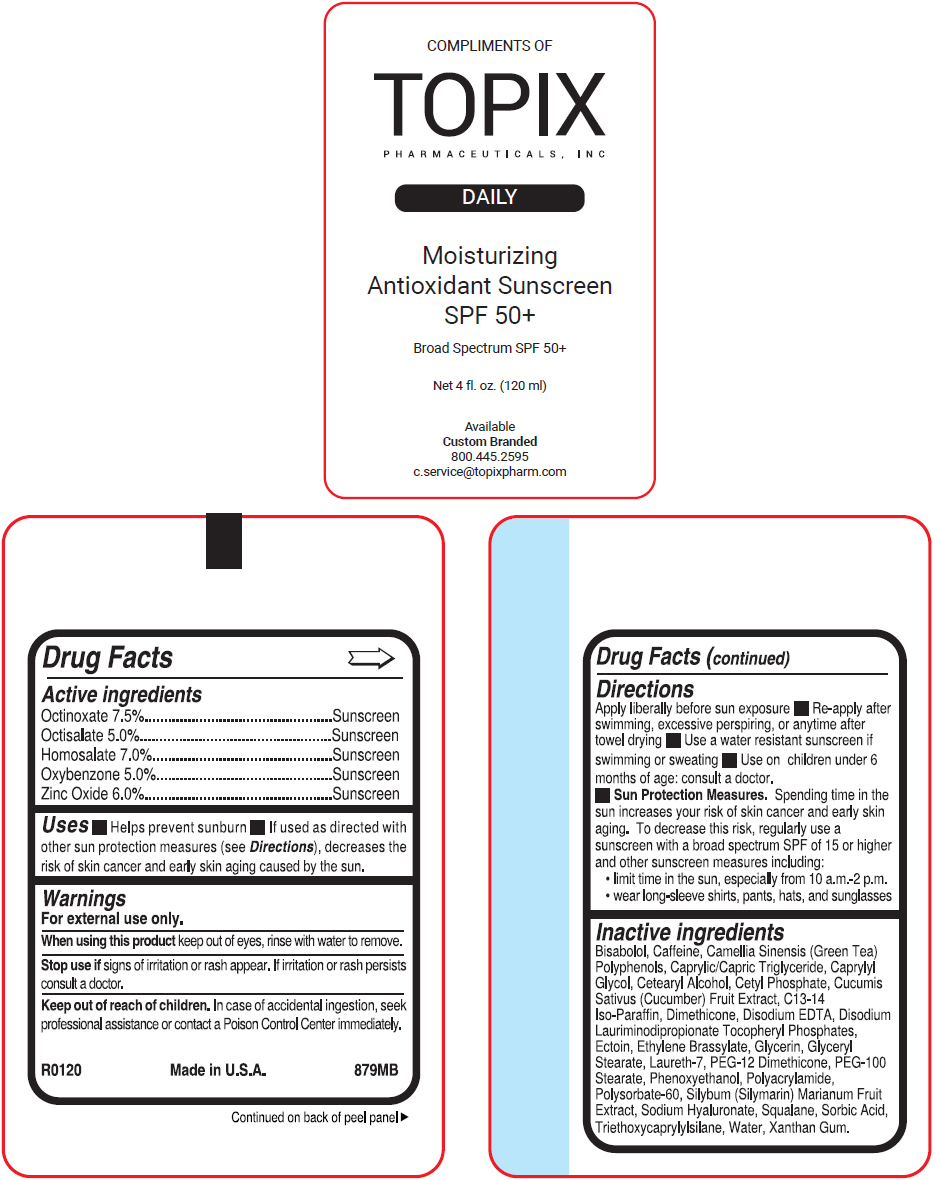 DRUG LABEL: Moisturizing Antioxidant
NDC: 51326-879 | Form: SPRAY
Manufacturer: Topiderm, Inc.
Category: otc | Type: HUMAN OTC DRUG LABEL
Date: 20260105

ACTIVE INGREDIENTS: OCTISALATE 50 mg/1 mL; OCTINOXATE 75 mg/1 mL; OXYBENZONE 50 mg/1 mL; HOMOSALATE 70 mg/1 mL; ZINC OXIDE 60 mg/1 mL
INACTIVE INGREDIENTS: .ALPHA.-BISABOLOL, (+)-; CAFFEINE; GREEN TEA LEAF; MEDIUM-CHAIN TRIGLYCERIDES; CAPRYLYL GLYCOL; CETOSTEARYL ALCOHOL; CETYL PHOSPHATE; CUCUMBER; C13-14 ISOPARAFFIN; DIMETHICONE 200; EDETATE DISODIUM; DISODIUM LAURIMINODIPROPIONATE; DISODIUM LAURIMINODIPROPIONATE TOCOPHERYL PHOSPHATES; ECTOINE; ETHYLENE BRASSYLATE; GLYCERIN; GLYCERYL MONOSTEARATE; LAURETH-7; PEG-12 DIMETHICONE (300 CST); PEG-100 MONOSTEARATE; PHENOXYETHANOL; POLYACRYLAMIDE (10000 MW); POLYSORBATE 60; MILK THISTLE; HYALURONATE SODIUM; SQUALANE; SORBIC ACID; TRIETHOXYCAPRYLYLSILANE; WATER; XANTHAN GUM

Moisturizing Antioxidant
SPF 50

Drug Facts

ACTIVE INGREDIENT

PURPOSE

Active ingredients
Octinoxate 7.5% | Sunscreen
Octisalate 5.0% | Sunscreen
Homosalate 7.0% | Sunscreen
Oxybenzone 5.0% | Sunscreen
Zinc Oxide 6.0% | Sunscreen

Uses

- Helps prevent sunburn
- If used as directed with other sun protection measures (see Directions), decreases the risk of skin cancer and early skin aging caused by the sun.

Warnings

For external use only.

When using this product keep out of eyes, rinse with water to remove.

Stop use if signs of irritation or rash appear. If irritation or rash persists consult a doctor.

Keep out of reach of children. In case of accidental ingestion, seek professional assistance or contact a Poison Control Center immediately.

Directions

Apply liberally before sun exposure

- Re-apply after swimming, excessive perspiring, or anytime after towel drying
- Use a water resistant sunscreen if swimming or sweating
- Use on children under 6 months of age: consult a doctor.
- Sun Protection Measures. Spending time in the sun increases your risk of skin cancer and early skin aging. To decrease this risk, regularly use a sunscreen with a broad spectrum SPF of 15 or higher and other sunscreen measures including:
  - limit time in the sun, especially from 10 a.m.-2 p.m.
  - wear long-sleeve shirts, pants, hats, and sunglasses

Inactive ingredients

Bisabolol, Caffeine, Camellia Sinensis (Green Tea) Polyphenols, Caprylic/Capric Triglyceride, Caprylyl Glycol, Cetearyl Alcohol, Cetyl Phosphate, Cucumis Sativus (Cucumber) Fruit Extract, C13-14 Iso-Paraffin, Dimethicone, Disodium EDTA, Disodium Lauriminodipropionate Tocopheryl Phosphates, Ectoin, Ethylene Brassylate, Glycerin, Glyceryl Stearate, Laureth-7, PEG-12 Dimethicone, PEG-100 Stearate, Phenoxyethanol, Polyacrylamide, Polysorbate-60, Silybum (Silymarin) Marianum Fruit Extract, Sodium Hyaluronate, Squalane, Sorbic Acid, Triethoxycaprylylsilane, Water, Xanthan Gum.

PRINCIPAL DISPLAY PANEL - 120 ml Can Label

COMPLIMENTS OF
TOPIX
PHARMACEUTICALS, INC

DAILY

Moisturizing
Antioxidant Sunscreen
SPF 50+

Broad Spectrum SPF 50+

Net 4 fl. oz. (120 ml)

Available
Custom Branded
800.445.2595
c.service@topixpharm.com